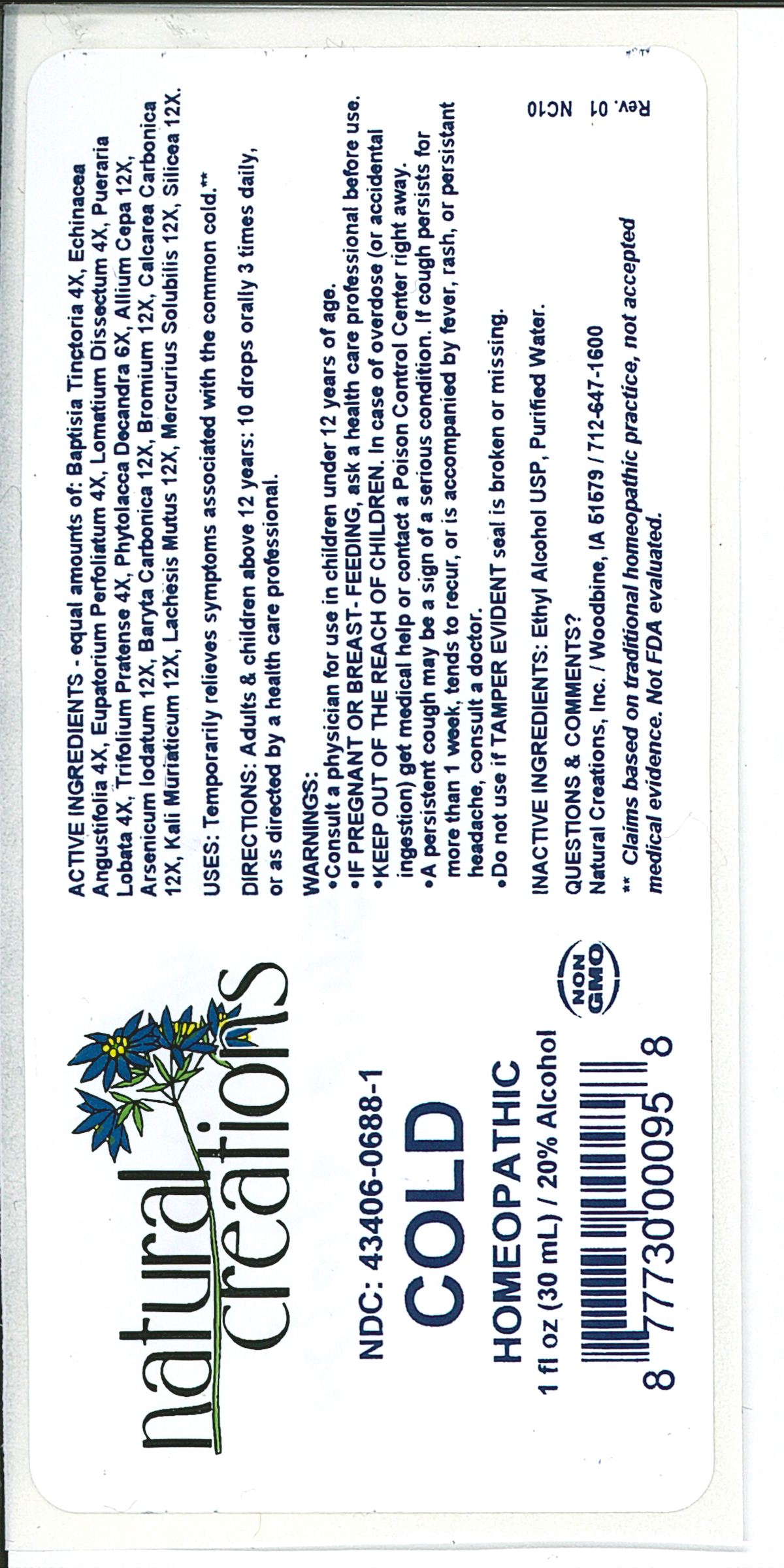 DRUG LABEL: Cold
NDC: 43406-0688 | Form: LIQUID
Manufacturer: Natural Creations, Inc
Category: homeopathic | Type: HUMAN OTC DRUG LABEL
Date: 20251120

ACTIVE INGREDIENTS: BAPTISIA TINCTORIA WHOLE 4 [hp_X]/1 mL; ECHINACEA ANGUSTIFOLIA WHOLE 4 [hp_X]/1 mL; EUPATORIUM PERFOLIATUM FLOWERING TOP 4 [hp_X]/1 mL; LOMATIUM DISSECTUM ROOT 4 [hp_X]/1 mL; PUERARIA MONTANA VAR. LOBATA WHOLE 4 [hp_X]/1 mL; TRIFOLIUM PRATENSE FLOWER 4 [hp_X]/1 mL; PHYTOLACCA AMERICANA ROOT 6 [hp_X]/1 mL; ONION 12 [hp_X]/1 mL; ARSENIC TRIIODIDE 12 [hp_X]/1 mL; BARIUM CARBONATE 12 [hp_X]/1 mL; BROMINE 12 [hp_X]/1 mL; OYSTER SHELL CALCIUM CARBONATE, CRUDE 12 [hp_X]/1 mL; POTASSIUM CHLORIDE 12 [hp_X]/1 mL; LACHESIS MUTA VENOM 12 [hp_X]/1 mL; MERCURIUS SOLUBILIS 12 [hp_X]/1 mL; SILICON DIOXIDE 12 [hp_X]/1 mL
INACTIVE INGREDIENTS: ALCOHOL; WATER

Cold

ACTIVE INGREDIENT

ACTIVE INGREDIENTS - equal amounts of: Baptisia Tinctoria 4X, Echinacea Angustifolia 4X, Eupatorium Perfoliatum 4X, Lomatium Dissectum 4X, Pueraria Lobata 4X, Trifolium Pratense 4X, Phytolacca Decandra 6X, Allium Cepa 12X, Arsenicum Iodatum 12X, Baryta Carbonica 12X, Bromium 12X, Calcarea Carbonica 12X, Kali Muriaticum 12X, Lachesis Mutus 12X, Mercurius Solubilis 12X, Silicea 12X

INDICATIONS AND USAGE

USES: Temporarily relieves symptoms associated with the common cold.**

PURPOSE

USES: Temporarily relieves symptoms associated with the common cold.**

DOSAGE AND ADMINISTRATION

DIRECTIONS: Adults & children above 12 years: 10 drops orally 3 times daily, or as directed by a health care professional.

KEEP OUT OF REACH OF CHILDREN

KEEP OUT OF THE REACH OF CHILDREN. In case of overdose (or accidental ingestion) get medical help or contact a Poison Control Center right away.

WARNINGS:

- Consult a physician for use in children under 12 years of age.
- IF PREGNANT OR BREAST-FEEDING, ask a health care professional before use.
- KEEP OUT OF THE REACH OF CHILDREN. In case of overdose (or accidental ingestion) get medical help or contact a Poison Control Center right away.
- A persistent cough may be a sign of a serious condition. If cough persists for more than 1 week, tends to recur, or is accompanied by fever, rash, or persistent headache, consult a doctor.
- Do not use if TAMPER EVIDENT seal is broken or missing.

INACTIVE INGREDIENTS: Ethyl Alcohol USP, Purified Water

QUESTIONS & COMMENTS?

Natural Creations, Inc. / Woodbine, IA 51579 / 712-647-1600

REFERENCES

**Claims based on traditional homeopathic practice, not accepted medical evidence. Not FDA evaluated.

PACKAGE LABEL

NDC:43406-0688-1

Cold

HOMEOPATHIC

1 fl oz (30mL) / 20% Alcohol